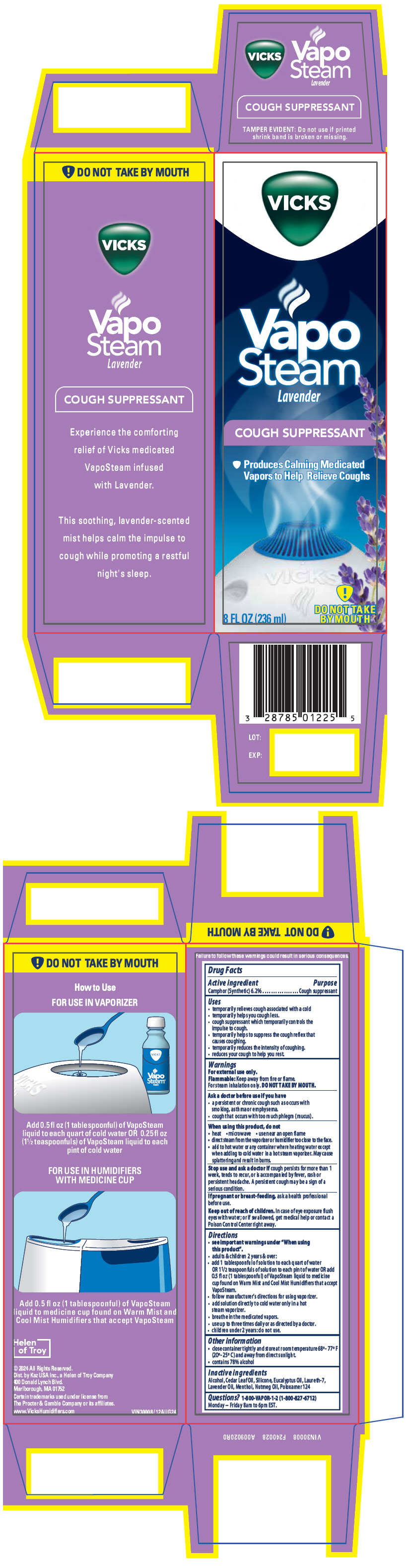 DRUG LABEL: Vicks Vaposteam Lavender
NDC: 69901-523 | Form: INHALANT
Manufacturer: Kaz USA, Inc
Category: otc | Type: HUMAN OTC DRUG LABEL
Date: 20241219

ACTIVE INGREDIENTS: CAMPHOR, (-)- 0.062 g/1 mL
INACTIVE INGREDIENTS: Alcohol; Cedar Leaf Oil; DIMETHICONE, UNSPECIFIED; Eucalyptus Oil; Laureth-7; Lavender Oil; MENTHOL, UNSPECIFIED FORM; Nutmeg Oil; Poloxamer 124

Vicks Vaposteam Lavender

Drug Facts

Active ingredient

Camphor (Synthetic) 6.2%

Purpose

Cough suppressant

Uses

- temporarily relieves cough associated with a cold
- temporarily helps you cough less.
- cough suppressant which temporarily controls the impulse to cough.
- temporarily helps to suppress the cough reflex that causes coughing.
- temporarily reduces the intensity of coughing.
- reduces your cough to help you rest.

Warnings

For external use only.

Flammable

Keep away from fire or flame.

For steam inhalation only. DO NOT TAKE BY MOUTH.

Ask a doctor before use if you have

- a persistent or chronic cough such as occurs with smoking, asthma or emphysema.
- cough that occurs with too much phlegm (mucus).

When using this product, do not

- heat
- microwave
- use near an open flame
- direct steam from the vaporizer or humidifier too close to the face.
- add to hot water or any container where heating water except when adding to cold water in a hot steam vaporizer. May cause splattering and result in burns.

Stop use and ask a doctor if cough persists for more than 1 week, tends to recur, or is accompanied by fever, rash or persistent headache. A persistent cough may be a sign of a serious condition.

PREGNANCY OR BREAST FEEDING

If pregnant or breast-feeding, ask a health professional before use.

Keep out of reach of children. In case of eye exposure flush eyes with water; or if swallowed, get medical help or contact a Poison Control Center right away.

Directions

- see important warnings under "When using this product".
- adults & children 2 years & over:
  - add 1 tablespoonful of solution to each quart of water OR 1½ teaspoonfuls of solution to each pint of water OR add 0.5 fl oz (1 tablespoonful) of VapoSteam liquid to medicine cup found on Warm Mist and Cool Mist Humidifiers that accept VapoSteam.
  - follow manufacturer's directions for using vaporizer.
  - add solution directly to cold water only in a hot steam vaporizer.
  - breathe in the medicated vapors.
  - use up to three times daily or as directed by a doctor.
- children under 2 years: do not use.

Other information

- close container tightly and store at room temperature 68°-77° F (20°-25° C) and away from direct sunlight.
- contains 78% alcohol

Inactive ingredients

Alcohol, Cedar Leaf Oil, Silicone, Eucalyptus Oil, Laureth-7, Lavender Oil, Menthol, Nutmeg Oil, Poloxamer 124

Questions?

1-800-VAPOR-1-2 (1-800-827-6712)

Monday – Friday 8am to 6pm EST.

Dist. by Kaz USA Inc., a Helen of Troy Company
400 Donald Lynch Blvd.
Marlborough, MA 01752

PRINCIPAL DISPLAY PANEL - 236 ml Bottle Box

VICKS

Vapo
Steam
Lavender

COUGH SUPPRESSANT

Produces Calming Medicated
Vapors to Help Relieve Coughs

8 FL OZ (236 ml)

DO NOT TAKE
BY MOUTH